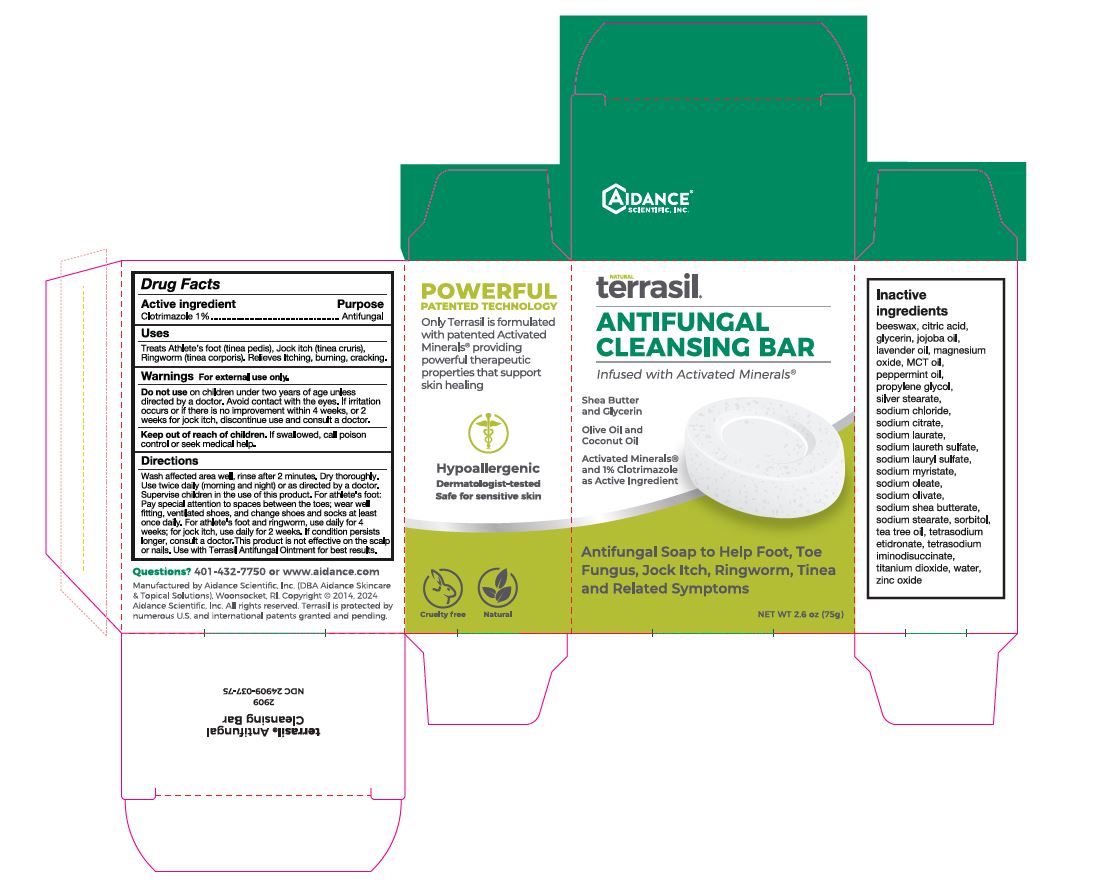 DRUG LABEL: terrasil Antifungal Cleansing Bar
NDC: 24909-037 | Form: SOAP
Manufacturer: Aidance Scientific, Inc, DBA Aidance Skincare & Topical Solutions
Category: otc | Type: HUMAN OTC DRUG LABEL
Date: 20241127

ACTIVE INGREDIENTS: CLOTRIMAZOLE 1 g/100 g
INACTIVE INGREDIENTS: YELLOW WAX; MEDIUM-CHAIN TRIGLYCERIDES; JOJOBA OIL; GLYCERIN; CITRIC ACID; LAVENDER OIL; MAGNESIUM OXIDE; PROPYLENE GLYCOL; PEPPERMINT OIL; SHEA BUTTER; SODIUM CHLORIDE; SODIUM CITRATE; SODIUM LAURATE; SODIUM LAURETH SULFATE; SODIUM LAURYL SULFATE; SODIUM MYRISTATE; SODIUM OLEATE; SODIUM OLIVATE; SODIUM STEARATE; SORBITOL; TEA TREE OIL; ETIDRONATE TETRASODIUM; TITANIUM DIOXIDE; WATER; ZINC OXIDE; SILVER STEARATE; TETRASODIUM IMINODISUCCINATE

24909-037 terrasil Antifungal Soap Bar

Active ingredient

Clotrimazole 1%

Pupose

Antifungal

Uses

Treats Athlete’s foot (tinea pedis), Jock itch (tinea cruris), Ringworm (tinea corporis). Relieves Itching, burning, cracking.

Warnings

For external use only.
Do not use on children under two years of age unless directed by a doctor. Avoid contact with the eyes. If irritation occurs or if there is no improvement within 4 weeks, or 2 weeks for jock itch, discontinue use and consult a doctor.

Keep out of reach of children.

OTHER SAFETY INFORMATION

If swallowed, call poison control or seek medical help.

Directions

Wash affected area well, rinse after 2 minutes. Dry thoroughly.
Use twice daily (morning and night) or as directed by a doctor.
Supervise children in the use of this product.
For athlete's foot: Pay special attention to spaces between the toes; wear well fitting, ventilated shoes, and change shoes and socks at least once daily.
For athlete's foot and ringworm, use daily for 4 weeks; for jock itch, use daily for 2 weeks. If condition persists longer, consult a doctor.
This product is not effective on the scalp or nails.
Use with Terrasil Antifungal Ointment for best results.

Inactive ingredients

beeswax, citric acid, glycerin, jojoba oil, lavender oil, magnesium oxide, MCT oil, peppermint oil, propylene glycol, silver stearate, sodium chloride, sodium citrate, sodium laurate, sodium laureth sulfate, sodium lauryl sulfate, sodium myristate, sodium oleate, sodium olivate, sodium shea butterate, sodium stearate, sorbitol, tea tree oil, tetrasodium etidronate, tetrasodium iminodisuccinate, titanium dioxide, water, zinc oxide

Questions?

401-432-7750 or www.aidance.com